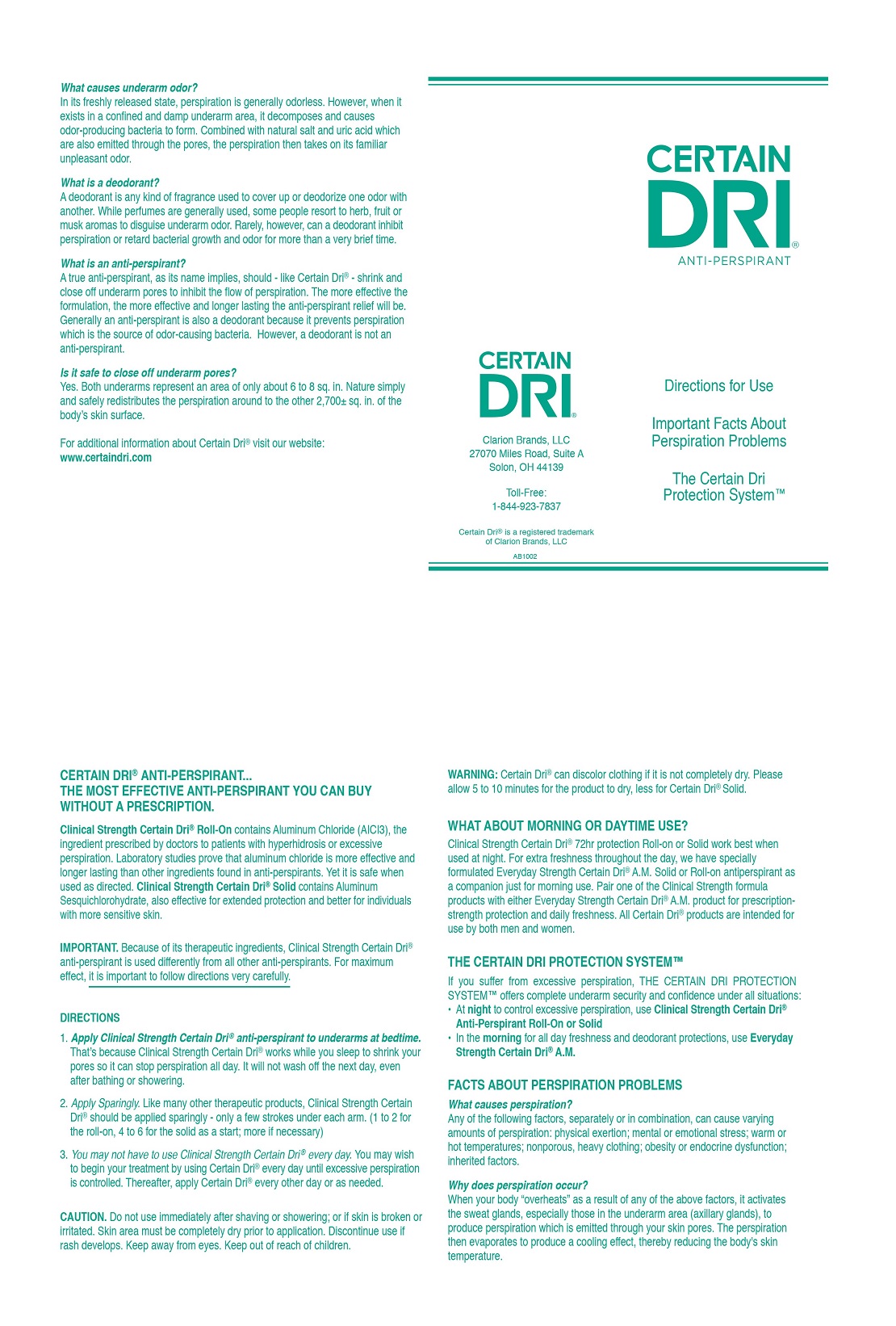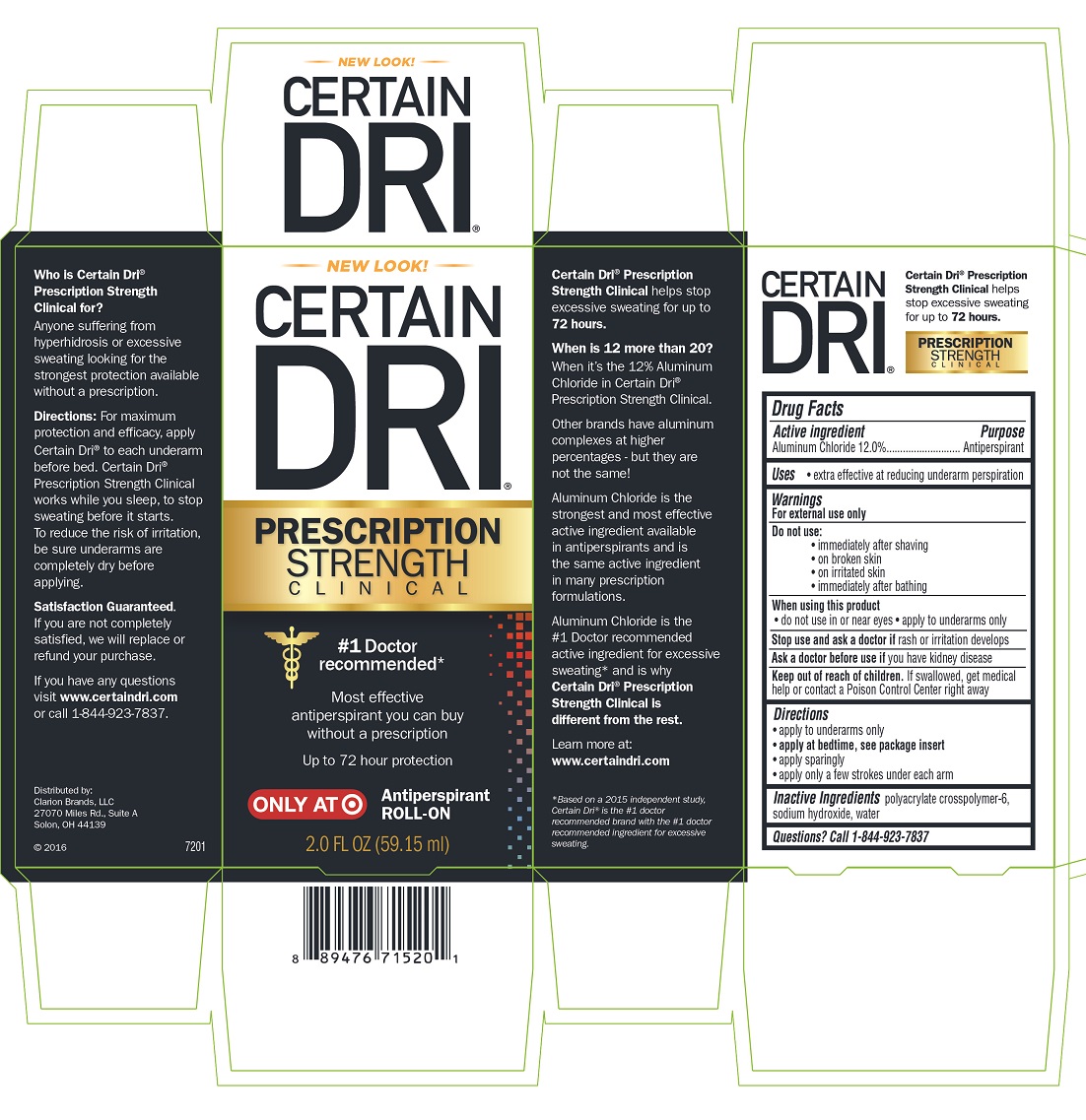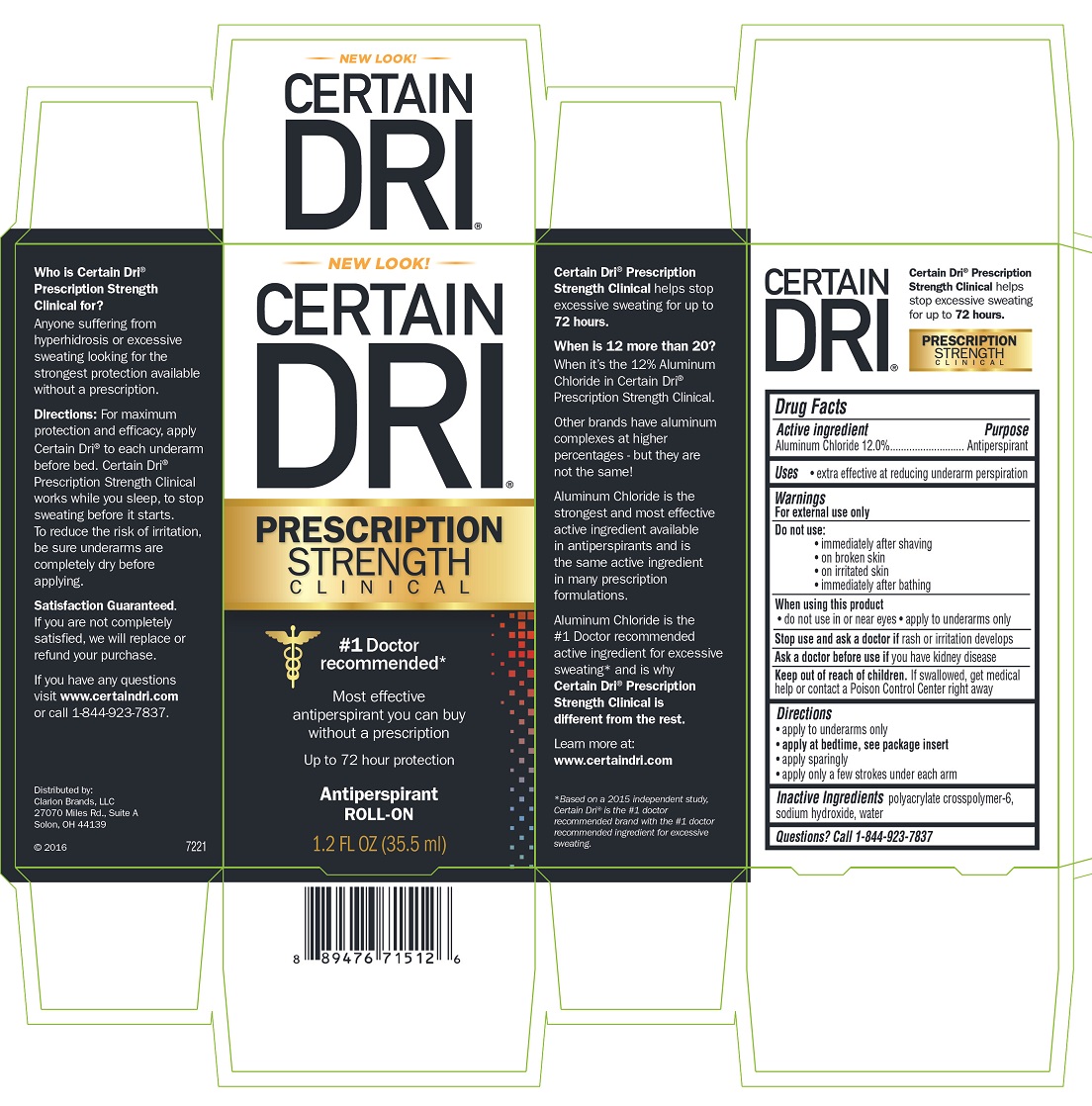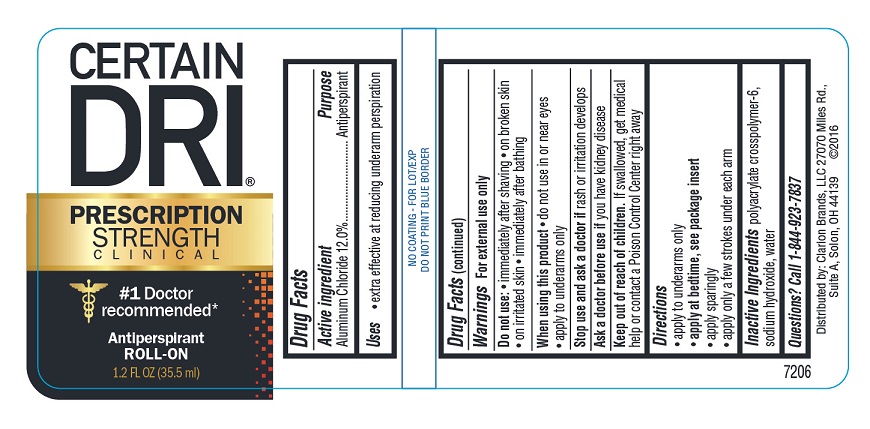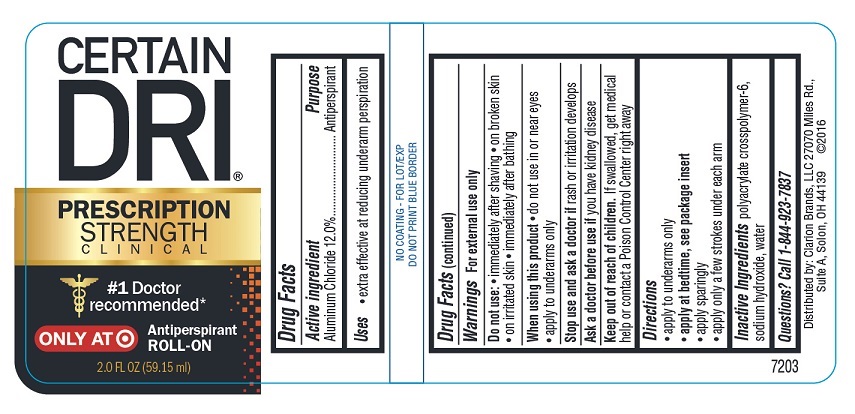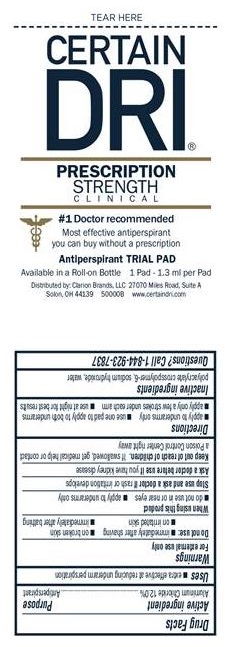 DRUG LABEL: CERTAIN DRI
NDC: 69693-715 | Form: LIQUID
Manufacturer: Clarion Brands, LLC
Category: otc | Type: HUMAN OTC DRUG LABEL
Date: 20251223

ACTIVE INGREDIENTS: ALUMINUM CHLORIDE 0.12 mg/1 mL
INACTIVE INGREDIENTS: SODIUM HYDROXIDE; WATER

Drug Facts

Active ingredient | Purpose
Aluminum Chloride 12.0% | Antiperspirant

Uses

- extra effective at reducing underarm perspiration

Warnings

For external use only

Do not use:

- immediately after shaving
- on broken skin
- on irritated skin
- immediately after bathing

When using this product

- do not use in or near eyes
- apply to underarms only

Stop use and ask a doctor ifrash or irritation develops

Ask a doctor before use ifyou have kidney disease

Keep out of reach of children.

If swallowed, get medical help or contact a Poison Control Center right away

Directions

- apply to underarms only
- apply at bedtime, see package insert
- apply sparingly
- apply only a few strokes under each arm

INACTIVE INGREDIENT

Inactive ingredientspolyacrylate crosspolymer-6, sodium hydroxide, water

Questions? Call 1-844-923-7837

Package Insert

CERTAIN DRI®ANTI-PERSPIRANT

Directions for Use

Important Facts About Perspiration Problems

The Certain Dri Protection™ System

CERTAIN DRI®

Clarion Brands, LLC
27070 Miles Road, Suite A
Solon, OH 44139

Toll-Free 1-844-923-7837

Certain Dri®is a registered trademark of Clarion Brands, LLC

AB1002

CERTAIN DRI®ANTI-PERSPIRANT...
THE MOST EFFECTIVE ANTI-PERSPIRANT YOU CAN BUY
WITHOUT A PRESCRIPTION.

Clinical Strength Certain Dri®Roll-On contains Aluminum Chloride (A1C13), the ingredient prescribed by doctors to patients with hyperhidrosis or excessive perspiration. Laboratory studies prove that aluminum chloride is more effective and longer lasting than other ingredients found in anti-perspirants. Yet it is safe when used as directed. Clinical Strength Certain Dri®Solid contains Aluminum Sesquichlorohydrate, also effective for extended protection and better for individuals with more sensitive skin.

IMPORTANT.Because of its therapeutic ingredients, Clinical Strength Certain Dri®anti-perspirant is used differently from all other anti-perspirants. For maximum effect, it is important to follow directions very carefully.

DIRECTIONS

1. Apply Clinical Strength Certain Dri®anti-perspirant to underarms at bedtime. That’s because Clinical Strength Certain Dri®works while you sleep to shrink your pores so it can stop perspiration all day. It will not wash off the next day, even after bathing or showering.
2. Apply Sparingly.Like many other therapeutic products, Clinical Strength Certain Dri®should be applied sparingly - only a few strokes under each arm. (1 to 2 for the roll-on, 4 to 6 for the solid as a start; more if necessary)
3. You may not have to use Clinical Strength Certain Dri®every day. You may wish to begin your treatment by using Certain Dri®every day until excessive perspiration is controlled. Thereafter, apply Certain Dri®every other day or as needed.

CAUTION.Do not use immediately after shaving or showering; or if skin is broken or irritated. Skin area must be completely dry prior to application. Discontinue use if rash develops. Keep away from eyes. Keep out of reach of children.

WARNING:Certain Dri®can discolor clothing if it is not completely dry. Please allow 5 to 10 minutes for the product to dry, less for Certain Dri®Solid.

WHAT ABOUT MORNING OR DAYTIME USE?

Clinical Strength Certain Dri®72hr protection Roll-on or Solid work best when used at night. For extra freshness throughout the day, we have specially formulated Everyday Strength Certain Dri®A.M. Solid or Roll-on antiperspirant as a companion just for morning use. Pair one of the Clinical Strength formula products with either Everyday Strength Certain Dri®A.M. product for prescription strength protection and daily freshness. All Certain Dri®products are intended for use by both men and women.

THE CERTAIN DRI PROTECTION SYSTEM™

If you suffer from excessive perspiration, THE CERTAIN DRI PROTECTION SYSTEM™ offers complete underarm security and confidence under all situations:

- At nightto control excessive perspiration, use Clinical Strength Certain Dri® Anti-Perspirant Roll-On or Solid
- In the morningfor all day freshness and deodorant protections, use Everyday Strength Certain Dri®A.M.

FACTS ABOUT PERSPIRATION PROBLEMS

What causes perspiration?
Any of the following factors, separately or in combination, can cause varying amounts of perspiration: physical exertion; mental or emotional stress; warm or hot temperatures; nonporous, heavy clothing; obesity or endocrine dysfunction; inherited factors.

Why does perspiration occur?
When your body “overheats” as a result of any of the above factors, it activates the sweat glands, especially those in the underarm area (axillary glands), to produce perspiration which is emitted through your skin pores. The perspiration then evaporates to produce a cooling effect, thereby reducing the body's skin temperature.

What causes underarm odor?
In its freshly released state, perspiration is generally odorless. However, when it exists in a confined and damp underarm area, it decomposes and causes odor-producing bacteria to form. Combined with natural salt and uric acid which are also emitted through the pores, the perspiration then takes on its familiar unpleasant odor.

What is a deodorant?
A deodorant is any kind of fragrance used to cover up or deodorize one odor with another. While perfumes are generally used, some people resort to herb, fruit or musk aromas to disguise underarm odor. Rarely, however, can a deodorant inhibit perspiration or retard bacterial growth and odor for more than a very brief time.

What is an anti-perspirant?
A true anti-perspirant, as its name implies, should - like Certain Dri®- shrink and close off underarm pores to inhibit the flow of perspiration. The more effective the formulation, the more effective and longer lasting the anti-perspirant relief will be. Generally an anti-perspirant is also a deodorant because it prevents perspiration which is the source of odor-causing bacteria. However, a deodorant is not an anti-perspirant.

Is it safe to close off underarm pores?
Yes. Both underarms represent an area of only about 6 to 8 sq. in. Nature simply and safely redistributes the perspiration around to the other 2,700± sq. in. of the body’s skin surface.

For additional information about Certain Dri®visit our website: www.certaindri.com

PRINCIPAL DISPLAY PANEL

NEW LOOK!
CERTAIN DRI®
PRESCRIPTION STRENGTH
CLINICAL
#1 Doctor recommended*
Most effective antiperspirant you can buy without a prescription
Up to 72 hour protection
Antiperspirant
ROLL-ON
2.0 FL OZ (59.15 ml)
Certain Dri®Prescription Strength Clinical helps stop excessive sweating for up to 72 hours.
When is 12 more than 20?
When it's the 12% Aluminum Chloride in Certain Dri®Prescription Strength Clinical.
Other brands have aluminum complexes at higher percentages - but they are not the same!
Aluminum Chloride is the strongest and most effective active ingredient available in antiperspirants and is the same active ingredient in may prescription formulations.
Aluminum Chloride is the #1 Doctor recommended active ingredient for excessive sweating* and is why Certain Dri®Prescription Strength Clinical is different from the rest.
Learn more at:
www.certaindri.com
* Based on a 2015 independent study, Certain Dri®is the #1 doctor recommended brand with the #1 doctor recommended ingredient for excessive sweating.
Who is Certain Dri®Prescription Strength Clinical for?
Anyone suffering from hyperhidrosis or excessive sweating looking for the strongest protection available without a prescription.
Directions:For maximum protection and efficacy, apply Certain Dri®to each underarm before bed. Certain Dri®Prescription Strength Clinical works while you sleep, to stop sweating before it starts. To reduce the risk of irritation, be sure underarms are completely dry before applying.
Satisfaction Guaranteed.
If you are not completely satisfied, we will replace or refund your purchase.
If you have any questions visit www.certaindri.com or call 1-844-923-7837
Distributed by:
Clarion Brands, LLC
27070 Miles Road, Suite A
Solon, OH 44139
©2016 7201
Certain Dri®Prescription Strength Clinical helps stop excessive sweating for up to 72 hours.

CERTAIN DRI®
PRESCRIPTION
STRENGTH
CLINICAL
#1 Doctor recommended*
Antiperspirant
ROLL-ON
2.0 FL OZ (59.15 ml)
Distributed by: Clarion Brands, LLC 27070 Miles Road,
Suite A, Solon, OH 44139 ©2016
7203

NEW LOOK!
CERTAIN DRI®
PRESCRIPTION STRENGTH
CLINICAL
#1 Doctor recommended*
Most effective antiperspirant you can buy without a prescription
Up to 72 hour protection
Antiperspirant
ROLL-ON
1.2 FL OZ (35.5 ml)
Certain Dri®Prescription Strength Clinical helps stop excessive sweating for up to 72 hours.
When is 12 more than 20?
When it's the 12% Aluminum Chloride in Certain Dri®Prescription Strength Clinical.
Other brands have aluminum complexes at higher percentages - but they are not the same!
Aluminum Chloride is the strongest and most effective active ingredient available in antiperspirants and is the same active ingredient in may prescription formulations.
Aluminum Chloride is the #1 Doctor recommended active ingredient for excessive sweating* and is why Certain Dri®Prescription Strength Clinical is different from the rest.
Learn more at:
www.certaindri.com
* Based on a 2015 independent study, Certain Dri®is the #1 doctor recommended brand with the #1 doctor recommended ingredient for excessive sweating.
Who is Certain Dri®Prescription Strength Clinical for?
Anyone suffering from hyperhidrosis or excessive sweating looking for the strongest protection available without a prescription.
Directions:For maximum protection and efficacy, apply Certain Dri®to each underarm before bed. Certain Dri®Prescription Strength Clinical works while you sleep, to stop sweating before it starts. To reduce the risk of irritation, be sure underarms are completely dry before applying.
Satisfaction Guaranteed.
If you are not completely satisfied, we will replace or refund your purchase.
If you have any questions visit www.certaindri.com or call 1-844-923-7837
Distributed by:
Clarion Brands, LLC
27070 Miles Road, Suite A
Solon, OH 44139
©2016 7221
Certain Dri®Prescription Strength Clinical helps stop excessive sweating for up to 72 hours.

CERTAIN DRI®
PRESCRIPTION
STRENGTH
CLINICAL
#1 Doctor recommended*
Antiperspirant
ROLL-ON
1.2 FL OZ (35.5 ml)
Distributed by: Clarion Brands, LLC 27070 Miles Road,
Suite A, Solon, OH 44139 ©2016
7206

TEAR HERE
CERTAIN DRI®
PRESCRIPTION STRENGTH
CLINICAL
#1 Doctor recommended
Most effective antiperspirant you can buy without a prescription
Antiperspirant TRIAL PAD
Available in a Roll-on Bottle
1 Pad - 1.3 ml per Pad
Distributed by Clarion Brands, LLC
27070 Miles Road, Suite A
Solon, OH 44139
500008
www.certaindri.com
Directions
■ apply to underarms only
■ use one pad to apply to both underarms
■ apply only a few strokes under each arm
■ use at night for best results

CERTAIN DRI®
ANTI-PERSPIRANT
Directions for Use
Important Facts About Perspiration Problems
The Certain Dri Protection System™
Clarion Brands, LLC
27070 Miles Road, Suite A
Solon, OH 44139
Toll-Free: 1-844-923-7837
Certain Dri®is a registered trademark of Clarion Brands, LLC
AB1002